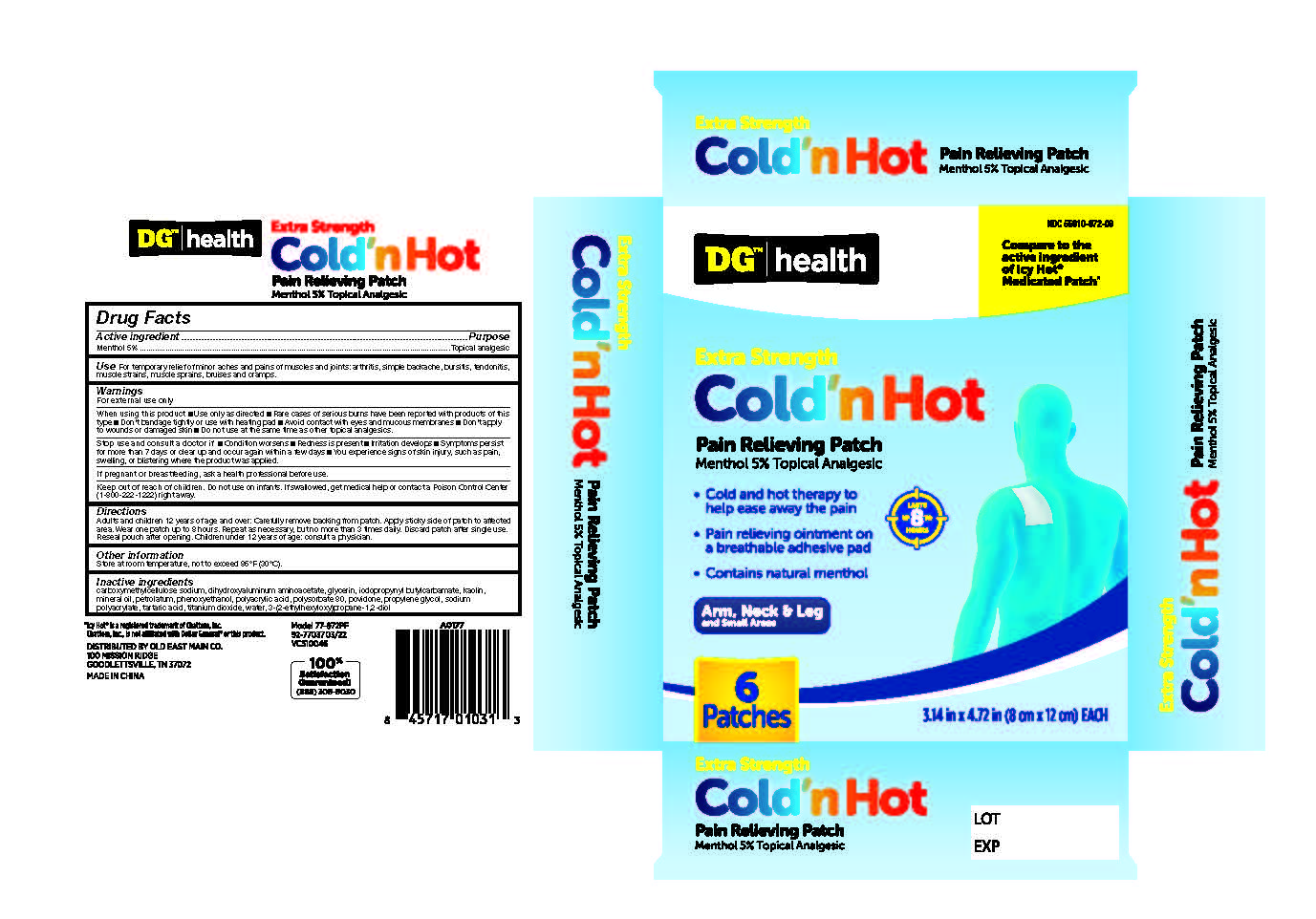 DRUG LABEL: Dollar General Cold-Hot Medicated Patches
NDC: 55910-972 | Form: PATCH
Manufacturer: DOLGENCORP, LLC
Category: otc | Type: HUMAN OTC DRUG LABEL
Date: 20250414

ACTIVE INGREDIENTS: MENTHOL 5 g/1 1
INACTIVE INGREDIENTS: PETROLATUM; MINERAL OIL; WATER; GLYCERIN; SODIUM POLYACRYLATE (8000 MW); DIHYDROXYALUMINUM AMINOACETATE; ETHYLHEXYLGLYCERIN; PHENOXYETHANOL; TITANIUM DIOXIDE; KAOLIN; POLYSORBATE 80; PROPYLENE GLYCOL; CARBOXYMETHYLCELLULOSE; TARTARIC ACID; POVIDONE, UNSPECIFIED; POLYACRYLIC ACID (8000 MW); IODOPROPYNYL BUTYLCARBAMATE

Dollar General Cold-Hot Medicated Patches

ACTIVE INGREDIENT

Active Ingredient ...............................................................................................Purpose
Menthol 5%...............................................................................................Topical Analgesic

INACTIVE INGREDIENT

carboxymethylcellulose sodium, Dihydroxyaluminum Aminoacetate, Glycerin, iodopropynyl butylcarbamate, Kaolin, Mineral Oil, Petrolatum, Phenoxyethanol, Polyacrylic Acid, Polysorbate 80, povidone, Propylene Glycol, Sodium Polyacrylate, Tartaric Acid, Titanium Dioxide, Water, 3-(2-ethylhexyloxy)propane-1,2-diol

KEEP OUT OF REACH OF CHILDREN

If swallowed, get medical help or contact a Poison Control

INDICATIONS & USAGE

Temporarily relieves minor pain associated with: ■ arthritis ■ simple backache ■ bursitis ■ tendonitis
■ muscle strains ■ muscle sprains ■ bruises ■ cramps

WARNINGS

For External Use Only.

DOSAGE & ADMINISTRATION

Adults and children over 12 years: Carefully remove backing from patch. Apply sticky side of patch to affected area.

Wear one patch up to 8 hours. Repeat as necessary, but no more than 4 times daily. Reseal pouch after opening.

Children 12 years or younger: Consult a physician.

PURPOSE

Topical Analgesic

When using this product

Use only as directed ■ Don’t bandage tightly or use with heating pad
■ Avoid contact with eyes and mucous membranes ■ Don’t apply to wounds or damaged skin.

Stop use and ask a doctor

If condition worsens ■ If redness is present ■ If irritation develops
■ If symptoms persist for more than 7 days or clear up and occur again within a few days.

If pregnant or breastfeeding

ask a health professional before use.